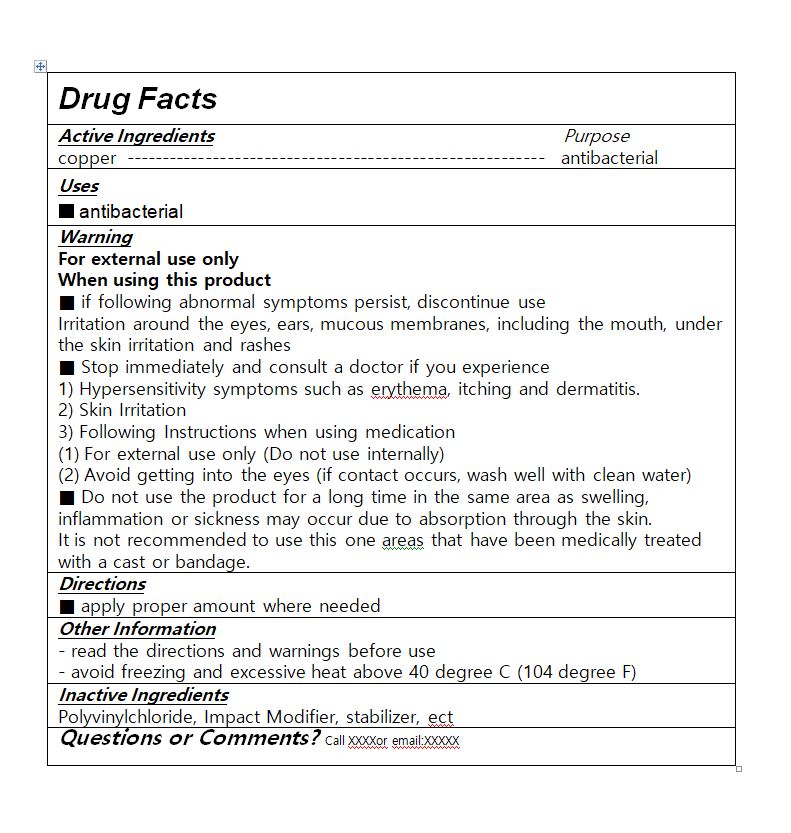 DRUG LABEL: Antibacterial PVC film
NDC: 79234-0002 | Form: FILM
Manufacturer: DH Investment Co Ltd
Category: otc | Type: HUMAN OTC DRUG LABEL
Date: 20200627

ACTIVE INGREDIENTS: COPPER 0.3 g/100 g
INACTIVE INGREDIENTS: HIGH DENSITY POLYETHYLENE

ACTIVE INGREDIENT

copper

INACTIVE INGREDIENT

Polyvinylchloride, Impact Modifier, stabilizer, etc

PURPOSE

Antibacterial

Keep out of reach of children

INDICATIONS AND USAGE

apply proper amount where needed

WARNINGS

For external use only

When using this product

■ if following abnormal symptoms persist, discontinue use

Irritation around the eyes, ears, mucous membranes, including the mouth, under the skin irritation and rashes

■ Stop immediately and consult a doctor if you experience

1) Hypersensitivity symptoms such as erythema, itching and dermatitis.

2) Skin Irritation

3) Following Instructions when using medication

(1) For external use only (Do not use internally)

(2) Avoid getting into the eyes (if contact occurs, wash well with clean water)

■ Do not use the product for a long time in the same area as swelling, inflammation or sickness may occur due to absorption through the skin.

It is not recommended to use this one areas that have been medically treated with a cast or bandage.

DOSAGE AND ADMINISTRATION

For external use only